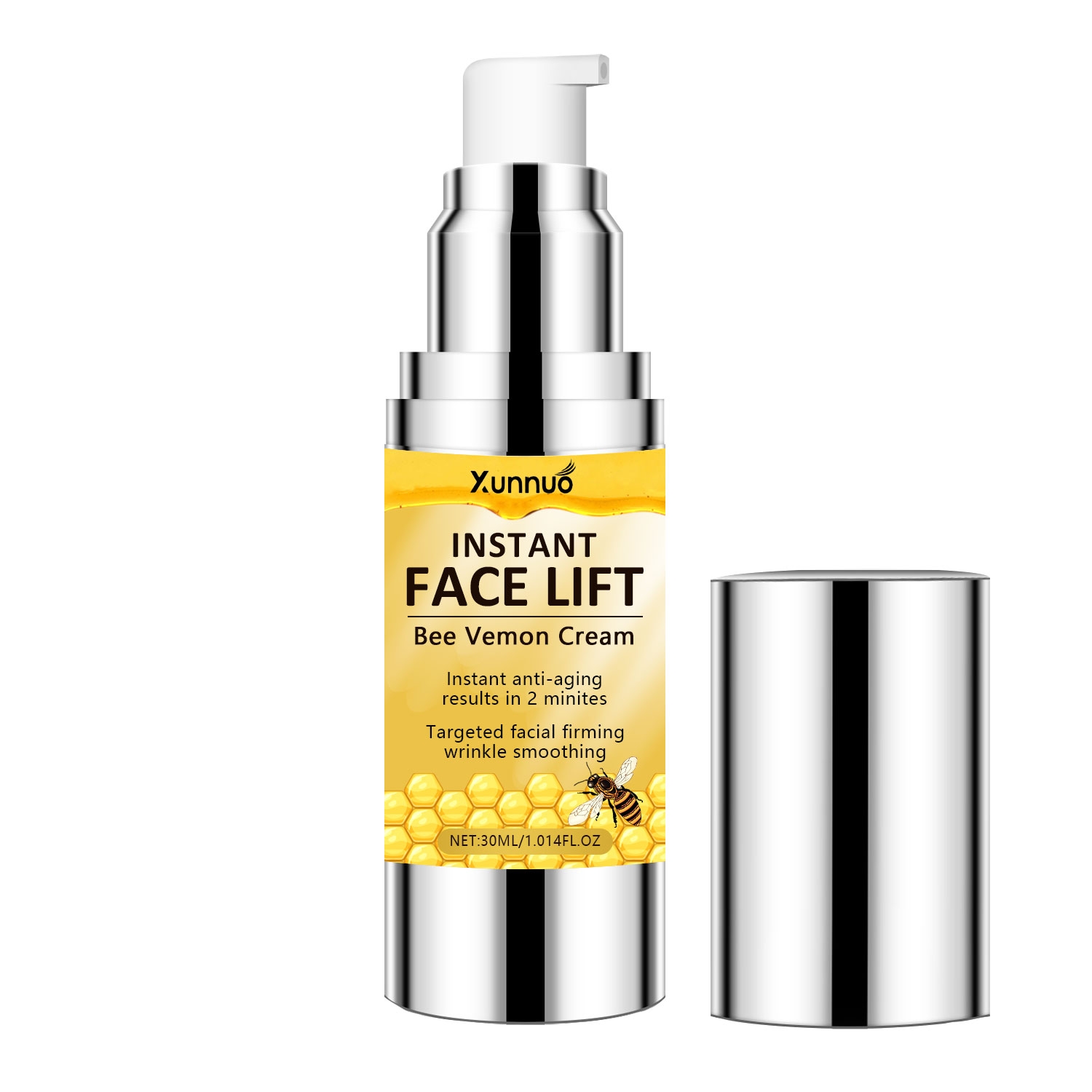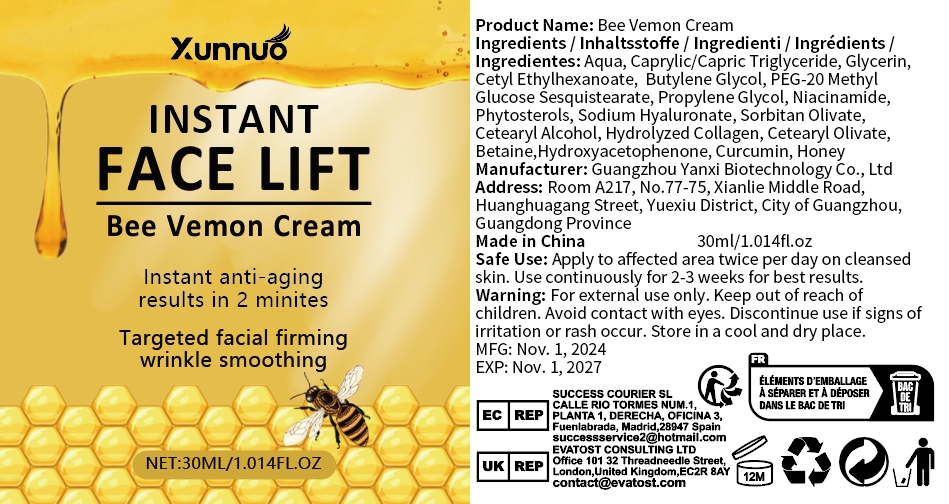 DRUG LABEL: Bee Vemon Cream
NDC: 84025-271 | Form: CREAM
Manufacturer: Guangzhou Yanxi Biotechnology Co., Ltd
Category: otc | Type: HUMAN OTC DRUG LABEL
Date: 20241123

ACTIVE INGREDIENTS: CAPRYLIC/CAPRIC TRIGLYCERIDE 3 mg/30 mL; CETYL ETHYLHEXANOATE 2 mg/30 mL
INACTIVE INGREDIENTS: WATER

DOSAGE AND ADMINISTRATION

Apply to affected area twice per day on cleansedskin.Use continuously for 2-3 weeks for best results

WARNINGS

Keep out of children

INACTIVE INGREDIENT

Aqua

INDICATIONS AND USAGE

For daily skin care

Keep out of children

PURPOSE

Targeted facial firming